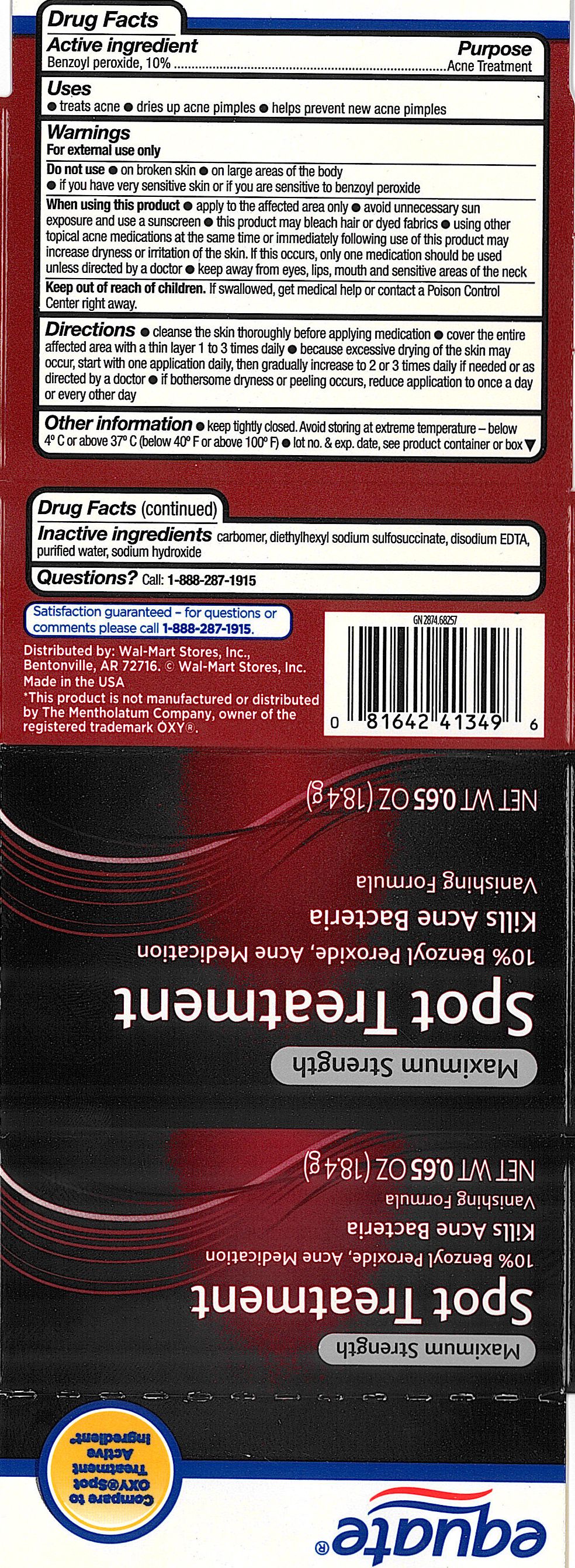 DRUG LABEL: Equate Maximum Strength Spot Treatment
NDC: 49035-022 | Form: GEL
Manufacturer: Wal-Mart Stores Inc
Category: otc | Type: HUMAN OTC DRUG LABEL
Date: 20110204

ACTIVE INGREDIENTS: BENZOYL PEROXIDE 135 mg/1 g
INACTIVE INGREDIENTS: WATER; DOCUSATE SODIUM; CARBOMER HOMOPOLYMER TYPE C; SODIUM HYDROXIDE; EDETATE SODIUM

drug facts

ACTIVE INGREDIENT

Section from Carton Label Follows:
Active ingredient Purpose
Benzoyl Peroxide, 10%...............................Acne Treatment

Uses
- Treats acne - dries up acne pimples - helps prevent new acne pimples

Keep out of reach of children. If swallowed, get medical help or contact a Poison
Control Center right away.

Directions

- cleanse the skin thoroughly before applying medication
- cover the entire affected area with a thin layer 1 to 3 times daily
- because excessive drying of the skin may occur, start with one application daily,
then gradually increase to 2 or 3 times daily if needed or as directed by a doctor
- if bothersome dryness or peeling occurs, reduce application too once a day or every other day
Other Information
- keep tightly closed. Avoid storing at extreme temperature - below
4 degrees C or above 37 degrees C (below 40 degrees F or above 100 degrees F)
- lot no. and exp. date, see product container or box
Questions?
Call 1-888-287-1915

Warnings
For external use only.
Do not use - on broken skin - on large areas of the body
- if you have very sensitive skin or if you are sensitive to benzoyl peroxide
When using this product - apply to the affected area only - avoid unnecessary sun
exposure and use a sunscreen - this product may bleach hair or dyed fabrics - using
other topical acne medications at the same time or immediately following use of this
product may increase dryness or irritation of the skin. If this occurs, only one medication
should be used unless directed by a doctor - keep away from eyes, lips, mouth and
sensitive areas of the neck
Keep out of reach of children. If swallowed, get medical help or contact a Poison
Control Center right away.

Directions

- cleanse the skin thoroughly before applying medication
- cover the entire affected area with a thin layer 1 to 3 times daily
- because excessive drying of the skin may occur, start with one application daily,
then gradually increase to 2 or 3 times daily if needed or as directed by a doctor
- if bothersome dryness or peeling occurs, reduce application too once a day or every other day

INACTIVE INGREDIENT

Inactive Ingredients carbomer, diethylhexyl sodium sulfosuccinate, disodium EDTA,
purified water, sodium hydroxide